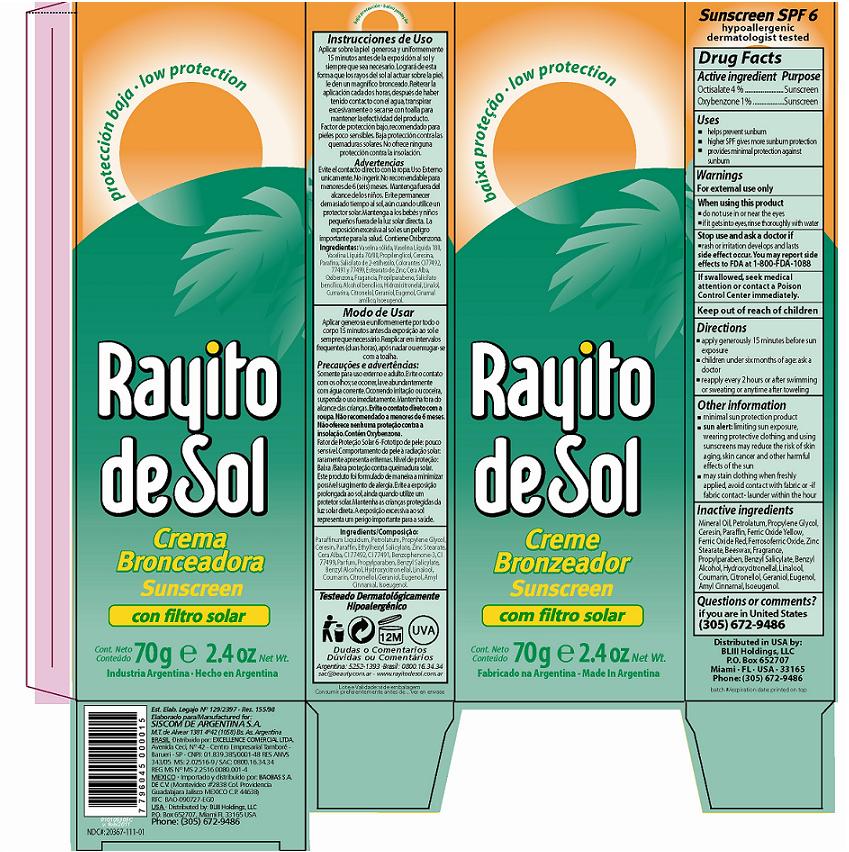 DRUG LABEL: Rayito de Sol Sunscreen SPF 6
NDC: 20367-111 | Form: CREAM
Manufacturer: Siscom de Argentina SA
Category: otc | Type: HUMAN OTC DRUG LABEL
Date: 20110214

ACTIVE INGREDIENTS: Octisalate 2.8 g/70 g; Oxybenzone 0.7 g/70 g
INACTIVE INGREDIENTS: Mineral Oil; PETROLATUM; Propylene Glycol; Ceresin; Paraffin; Zinc Stearate; YELLOW WAX; Propylparaben; Benzyl Salicylate; Benzyl Alcohol; Hydroxycitronellal; LINALOOL, DL-; Coumarin; .BETA.-CITRONELLOL, (+/-)-; Geraniol; Eugenol; .ALPHA.-AMYLCINNAMALDEHYDE; Isoeugenol; FERRIC OXIDE YELLOW; FERRIC OXIDE RED; FERROSOFERRIC OXIDE

Rayito de Sol Sunscreen SPF 6

Active ingredient

Octisalate 4%

Oxybenzone 1%

Purpose

Sunscreen

Sunscreen

Uses

- Helps prevent sunburn.
- Higher SPF gives more sunburn protection.
- Provides minimal protection against sunburn.

Warnings

For external use only.

When using this product

- do not use in or near the eyes
- if it gets into eyes rinse thoroughly with water

Stop use and ask a doctor if

- rash or irritation develops and lasts

Side effect occur. You may report side effects to FDA at 1-800-FDA-1088

If swallowed, seek medical attention or contact a Poison Control Center immediately.

Directions

- Apply generously 15 minutes before sun exposure.
- Children under six months of age: ask a doctor.
- Reapply every 2 hours or after swimming or sweating or anytime after towelling.

Other Information

- Minimal sun protection product.
- Sun alert: limiting sun exposure, wearing protective clothing, and using sunscreens my reduce the risk of skin aging, skin cancer and other harmful effects of the sun.
- May stain clothing when freshly applied. Avoid contact with fabric or if fabric contact, launder within the hour.

Inactive ingredients

Mineral Oil, Petrolatum, Propylene Glycol, Ceresin, Paraffin, CI 77492 (and) CI 77491 (and) CI 77499, Zinc Stearate, Cera Alba, Fragrance, Propylparaben, Benzyl Salicylate, Benzyl Alcohol, Hydroxycitronellal, Linalool, Coumarin, Citronellol, Geraniol, Eugenol, Amyl Cinnamal, Isoeugenol.

Questions or comments?

if you are in United States

(305) 672-9486

Principal Display Panel

Rayito de Sol
Sunscreen SPF 6
70g/2.4oz